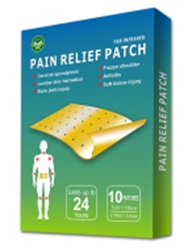 DRUG LABEL: Pain Relief Patch
NDC: 81484-201 | Form: PATCH
Manufacturer: Anhui Miao De Tang Pharmaceutical Co., Ltd.
Category: otc | Type: HUMAN OTC DRUG LABEL
Date: 20231114

ACTIVE INGREDIENTS: CAMPHOR (SYNTHETIC) 3.8 g/1 1; METHYL SALICYLATE 3.1 g/1 1; MENTHOL 5.2 g/1 1
INACTIVE INGREDIENTS: NATURAL LATEX RUBBER; LANOLIN; BORNEOL; PETROLATUM; ROSIN

Pain Relief Patch

Pain Relief Patchs

Active Ingredient(s)

Camphor 3.8g/patch
Menthol 5.2g/patch
Methyl Salicylate 3.1g/patch

Purpose

Topical Analgesic, Pain Relief Patch

Use

Use to the adjuvant treatment of pain caused by cervical spondylosis, frozen shoulder, lumbar disc herniation, rheumatoid arthritis, and bone or joint or soft tissue injury.

Warnings

For external use only.

Do not use

- On wounds or damaged skin
- With a heating pad
- If you are allergic to any ingredients of this product

WHEN USING

- Use only as directed
- Avoid contact with eyes, mucous membranes or rashes
- Do not bandage tightly
- Do not use at the same time as other topical analgesics
- Dispose of used patch in manner that keeps product away from children and pets. Used patches still contain the drug product that can produce serious adverse effects if a child or pet chews or ingests this patch.

STOP USE

- If rash, itching or excessive skin irritation develops
- If condition worsens
- if symptoms last more than 7 days or clear up and occur again with a few days

Keep out of reach of children. If swallowed, get medical help or contact a Poison Control Center right away.

Directions

- For temporary relief of minor aches and pains.

Other information

- Store in clean, dry place outside of direct sunlight. Protect from excessive moisture.

Inactive ingredients

Colophony
Lanolin
Borneol
Vaseline
Natural Rubber